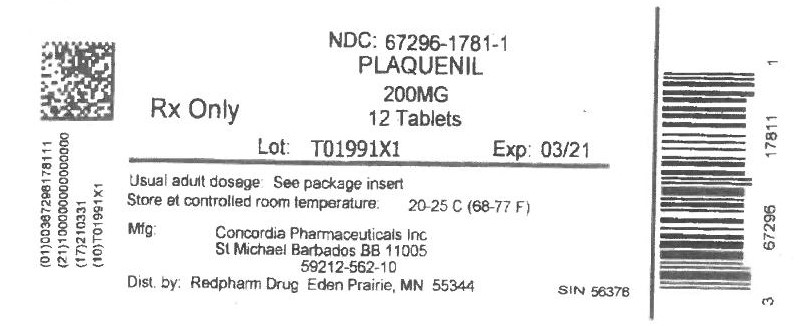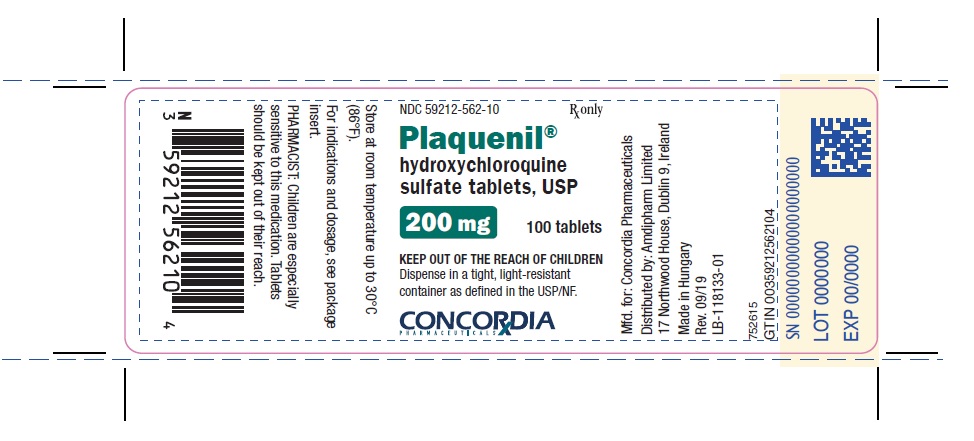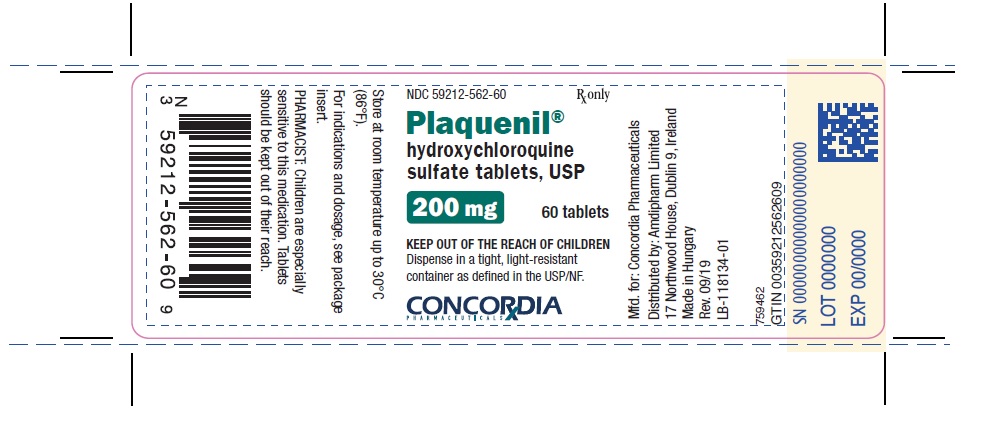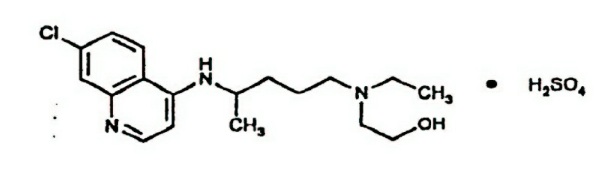 DRUG LABEL: Plaquenil
NDC: 67296-1781 | Form: TABLET
Manufacturer: RedPharm Drug, Inc.
Category: prescription | Type: HUMAN PRESCRIPTION DRUG LABEL
Date: 20220121

ACTIVE INGREDIENTS: HYDROXYCHLOROQUINE SULFATE 200 mg/1 1
INACTIVE INGREDIENTS: CALCIUM PHOSPHATE, DIBASIC, ANHYDROUS; HYPROMELLOSE 2910 (6 MPA.S); MAGNESIUM STEARATE; POLYETHYLENE GLYCOL 400; POLYSORBATE 80; STARCH, CORN; TITANIUM DIOXIDE; CARNAUBA WAX; SHELLAC; FERROSOFERRIC OXIDE

PLAQUENIL 200mg tab

DESCRIPTION

PLAQUENIL® (hydroxychloroquine sulfate) is a white or practically white, crystalline powder, freely soluble in water; practically insoluble in alcohol, chloroform, and in ether. The chemical name for hydroxychloroquine sulfate is 2-[[4-[(7-Chloro-4-quinolyl)amino]pentyl]ethylamino] ethanol sulfate (1:1). Its structural formula is:

The molecular weight of hydroxychloroquine sulfate is 433.95, and molecular formula is C18H26ClN3O.H2SO4.

PLAQUENIL (hydroxychloroquine sulfate) tablets contain 200 mg hydroxychloroquine sulfate, equivalent to 155 mg base, and are for oral administration.

Inactive Ingredients: Dibasic calcium phosphate USP, hypromellose USP, magnesium stearate NF, polyethylene glycol 400 NF, polysorbate 80 NF, corn starch, titanium dioxide USP, carnauba wax NF, shellac NF, black iron oxide NF.

CLINICAL PHARMACOLOGY

PHARMACOKINETICS

Pharmacokinetics: Following a single 200 mg oral dose of PLAQUENIL to healthy male volunteers, the mean peak blood concentration of hydroxychloroquine was 129.6 ng/mL, reached in 3.26 hours with a half-life of 537 hours (22.4 days). In the same study, the plasma peak concentration was 50.3 ng/mL reached in 3.74 hours with a half-life of 2963 hours (123.5 days). Urine hydroxychloroquine levels were still detectable after 3 months with approximately 10% of the dose excreted was parent drug. Results following a single dose of a 200 mg tablet versus i.v. infusion (155 mg), demonstrated a half-life of about 40 days and a large volume of distribution. Peak blood concentrations of metabolites were observed at the same time as peak levels of hydroxycholoquine. The mean fraction of the dose absorbed was 0.74. After administration of single 155 mg and 310 mg intravenous doses, peak blood concentrations ranged from 1161 ng/mL to 2436 ng/mL (mean 1918 ng/mL) following the 155 mg infusion and 6 months following the 3as10 mg infusion. Pharmacokinetic parameters were not significantly different over the therapeutic dose range of 155 mg and 310 mg indicating linear kinetics.

Following chronic oral administration of hydroxychloroquine, significant levels of three metabolites, desethylhydroxychloroquine (DHCQ), desethylchloroquine (DCQ), and bidesethylhydroxychloroquine (BDCQ) have been found in plasma and blood, with DHCQ being the major metabolite. The absorption half-life was approximately 3 to 4 hours and the terminal half-life ranged from 40 to 50 days. The long half-life can be attributed to extensive tissue uptake rather than through decreased excretion. Peak plasma levels of hydroxychloroquine were seen in about 3 to 4 hours. Renal clearance in rheumatoid arthritis (RA) patients taking PLAQUENIL for at least six months seemed to be similar to that of the single dose studies in volunteers, suggesting that no change occurs with chronic dosing. Range for renal clearance of unchanged drug was approximately 16 to 30% and did not correlate with creatinine clearance; therefore, a dosage adjustment is not required for patients with renal impairment. In RA patients, there was large variability as to the fraction of the dose absorbed (i.e. 30 to 100%), and mean hydroxychloroquine levels were significantly higher in patients with less disease activity. Cellular levels of patients on daily hydroxychloroquine have been shown to be higher in mononuclear cells than polymorphonuclear leucocytes.

Microbiology - Malaria

Mechanism of action: The precise mechanism by which hydroxychloroquine exhibits activity against Plasmodium is not known. Hydroxychloroquine, like chloroquine, is a weak base and may exert its effect by concentrating in the acid vesicles of the parasite and by inhibiting polymerization of heme. It can also inhibit certain enzymes by its interaction with DNA.

Activity in vitro and in Clinical Infections: Hydroxychloroquine is active against the erythrocytic forms of chloroquine sensitive strains of Plasmodium falciparum, Plasmodium malariae, Plasmodium ovale, and Plasmodium vivax. Hydroxychloroquine is not active against the gametocytes and exoerythrocytic forms including the hypnozoite stage (P. vivax and P. ovale) of the Plasmodium parasites.

Drug Resistance: P. falciparum strains exhibiting reduced susceptibility to chloroquine also show reduced susceptibility to hydroxychloroquine.

Resistance of Plasmodium parasites to chloroquine is widespread (see INDICATIONS AND USAGE – Malaria).

Patients in whom chloroquine or hydroxychloroquine have failed to prevent or cure clinical malaria or parasitemia, or patients who acquired malaria in a geographic area where chloroquine resistance is known to occur should be treated with another form of antimalarial therapy (see INDICATIONS AND USAGE – Malariaand WARNINGS).

Rheumatoid Arthritis and Systemic Lupus Erythematosus

Mechanism of action: The mechanisms underlying the anti-inflammatory and immunomodulatory effects of PLAQUENIL are unknown

INDICATIONS AND USAGE

Malaria

PLAQUENIL is indicated for the treatment of uncomplicated malaria due to P. falciparum, P. malariae, P. ovale, and P. vivax.

PLAQUENIL is indicated for the prophylaxis of malaria in geographic areas where chloroquine resistance is not reported.

Limitations of Use in Malaria
• PLAQUENIL is not recommended for the treatment of complicated malaria.
• PLAQUENIL is not effective against chloroquine or hydroxychloroquine-resistant strains of Plasmodium species (see CLINICAL PHARMACOLOGY – Microbiology). PLAQUENIL is not recommended for the treatment of malaria acquired in geographic areas where chloroquine resistance occurs or when the Plasmodium species has not been identified.
• PLAQUENIL is not recommended for malaria prophylaxis in geographic areas where chloroquine resistance occurs.
• PLAQUENIL does not prevent relapses of P. vivax or P. ovale because it is not active against the hypnozoite forms of these parasites. For radical cure of P. vivax and P. ovale infections, concomitant therapy with an 8-aminoquinoline compound is necessary (see CLINICAL PHARMACOLOGY – Microbiology).

Prior to prescribing PLAQUENIL for the treatment or prophylaxis of malaria, consult the Centers for Disease Control and Prevention (CDC) Malaria website (http://www.cdc.gov/malaria).

Lupus Erythematosus

PLAQUENIL is indicated for the treatment of chronic discoid lupus erythematosus and systemic lupus erythematosus in adults.

Rheumatoid Arthritis

PLAQUENIL is indicated for the treatment of acute and chronic rheumatoid arthritis in adults.

CONTRAINDICATIONS

Use of PLAQUENIL is contraindicated in patients with known hypersensitivity to 4-aminoquinoline compounds.

WARNINGS

Resistant strains of malaria: PLAQUENIL is not effective against chloroquine-resistant strains of P. falciparum (see CLINICAL PHARMACOLOGY – Microbiology).

Ocular: Irreversible retinal damage has been observed in some patients who had received hydroxychloroquine sulfate. Significant risk factors for retinal damage include daily doses of hydroxychloroquine sulfate greater than 6.5 mg/kg (5 mg/kg base) of actual body weight, durations of use greater than five years, subnormal glomerular filtration, use of some concomitant drug products such as tamoxifen citrate and concurrent macular disease.

A baseline ocular examination is recommended within the first year of starting PLAQUENIL. The baseline exam should include: best corrected distance visual acuity (BCVA), an automated threshold visual field (VF) of the central 10 degrees (with retesting if an abnormality is noted), and spectral domain ocular coherence tomography (SD-OCT).

For individuals with significant risk factors (daily dose of hydroxychloroquine sulfate greater than 5.0 mg/kg base of actual body weight, subnormal glomerular filtration, use of tamoxifen citrate or concurrent macular disease) monitoring should include annual examinations which include BCVA, VF and SD-OCT. For individuals without significant risk factors, annual exams can usually be deferred until five years of treatment.

In individuals of Asian descent, retinal toxicity may first be noticed outside the macula. In patients of Asian descent, it is recommended that visual field testing be performed in the central 24 degrees instead of the central 10 degrees.

It is recommended that hydroxychloroquine be discontinued if ocular toxicity is suspected and the patient should be closely observed given that retinal changes (and visual disturbances) may progress even after cessation of therapy.

Cardiac Effects, including Cardiomyopathy and QT prolongation: Postmarketing cases of life-threatening and fatal cardiomyopathy have been reported with use of PLAQUENIL as well as with use of chloroquine. Patients may present with atrioventricular block, pulmonary hypertension, sick sinus syndrome or with cardiac complications. ECG findings may include atrioventricular, right or left bundle branch block. Signs or symptoms of cardiac compromise have appeared during acute and chronic treatment. Clinical monitoring for signs and symptoms of cardiomyopathy is advised, including use of appropriate diagnostic tools such as ECG to monitor patients for cardiomyopathy during PLAQUENIL therapy. Chronic toxicity should be considered when conduction disorders (bundle branch block/atrio-ventricular heart block) or biventricular hypertrophy are diagnosed. If cardiotoxicity is suspected, prompt discontinuation of PLAQUENIL may prevent life-threatening complications.

PLAQUENIL prolongs the QT interval. Ventricular arrhythmias and torsades de pointes have been reported in patients taking PLAQUENIL (see OVERDOSAGE). Therefore, PLAQUENIL should not be administered with other drugs that have the potential to prolong the QT interval (see DRUG INTERACTIONS).

Worsening of psoriasis and porphyria: Use of PLAQUENIL in patients with psoriasis may precipitate a severe attack of psoriasis. When used in patients with porphyria the condition may be exacerbated. The preparation should not be used in these conditions unless in the judgment of the physician the benefit to the patient outweighs the possible hazard.

Proximal Myopathy and Neuropathy: Skeletal muscle myopathy or neuropathy leading to progressive weakness and atrophy of proximal muscle groups, depressed tendon reflexes, and abnormal nerve conduction, have been reported. Muscle and nerve biopsies have been associated with curvilinear bodies and muscle fiber atrophy with vacuolar changes. Assess muscle strength and deep tendon reflexes periodically in patients on long-term therapy with PLAQUENIL.

Neuropsychiatric events, including suicidality: Suicidal behavior has been rarely reported in patients treated with PLAQUENIL.

Hypoglycemia: PLAQUENIL has been shown to cause severe hypoglycemia including loss of consciousness that could be life threatening in patients treated with or without antidiabetic medications (see DRUG INTERACTIONS and ADVERSE REACTIONS). Patients treated with PLAQUENIL should be warned about the risk of hypoglycemia and the associated clinical signs and symptoms. Patients presenting with clinical symptoms suggestive of hypoglycemia during treatment with PLAQUENIL should have their blood glucose checked and treatment reviewed as necessary.

PRECAUTIONS

General: Use with caution in patients with gastrointestinal, neurological, or blood disorders, and in those with a sensitivity to quinine.

Hepatic/Renal Disease: Antimalarial compounds should be used with caution in patients with hepatic disease or alcoholism, or in conjunction with known hepatotoxic drugs. A reduction in dosage may be necessary in patients with hepatic or renal disease, as well as in those taking medicines known to affect these organs.

Hematologic Effects/Laboratory Tests: Antimalarial compounds should be used with caution in patients with hepatic disease or alcoholism or in conjunction with known hepatotoxic drugs. Periodic blood cell counts should be performed if patients are given prolonged therapy. If any severe blood disorder such as aplastic anemia, agranulocytosis, leukopenia, or thrombocytopenia, appears which is not attributable to the disease under treatment, consider discontinuation of PLAQUENIL.

PLAQUENIL should be administered with caution in patients having glucose-6-phosphate dehydrogenase (G-6-PD) deficiency.

Dermatologic Effects: Dermatologic reactions to PLAQUENIL may occur and, therefore, proper care should be exercised when it is administered to any patient receiving a drug with a significant tendency to produce dermatitis.

Drug Interactions

Digoxin: Concomitant PLAQUENIL and digoxin therapy may result in increased serum digoxin levels: serum digoxin levels should be closely monitored in patients receiving combined therapy.

Insulin or antidiabetic drugs: As PLAQUENIL may enhance the effects of a hypoglycemic treatment, a decrease in doses of insulin or antidiabetic drugs may be required.

Drugs that prolong QT interval and other arrhythmogenic drugs: PLAQUENIL prolongs the QT interval and should not be administered with other drugs that have the potential to induce cardiac arrhythmias. Also, there may be an increased risk of inducing ventricular arrhythmias if PLAQUENIL is used concomitantly with other arrhythmogenic drugs.

Mefloquine and other drugs known to lower the convulsive threshold: PLAQUENIL can lower the convulsive threshold. Co-administration of PLAQUENIL with other antimalarials known to lower the convulsion threshold (e.g., mefloquine) may increase the risk of convulsions.

Antiepileptics: The activity of antiepileptic drugs might be impaired if co-administered with PLAQUENIL.

Methotrexate: Combined use of methotrexate with PLAQUENIL has not been studied and may increase the incidence of adverse effects.

Cyclosporin: An increased plasma cyclosporin level was reported when cyclosporin and PLAQUENIL were co-administered.

The following interactions have been observed on treatment with the structurally related substance chloroquine phosphate, and therefore cannot be ruled out for hydroxychloroquine.

Praziquantel: Chloroquine has been reported to reduce the bioavailability of praziquantel.

Antacids and kaolin: Antacids and kaolin can reduce absorption of chloroquine; an interval of at least 4 hours between intake of these agents and chloroquine should be observed.

Cimetidine: Cimetidine can inhibit the metabolism of chloroquine, increasing its plasma level. Concomitant use of cimetidine should be avoided.

Ampicillin: In a study of healthy volunteers, chloroquine significantly reduced the bioavailability of ampicillin.

PATIENT COUNSELING INFORMATION

Information for Patients: Patients should be informed of the early signs and symptoms of toxicity such as rash or visual changes. Patients must see their physicians promptly in case of the appearance of these or of any unusual effects. Periodic laboratory tests may be recommended in some patients. Patients should be fully informed of the potential risks of the use of PLAQUENIL, especially in pregnancy and in children.

Carcinogenesis, mutagenesis, impairment of fertility:
Long-term studies in animals have not been conducted to evaluate the carcinogenic potential of PLAQUENIL.

The mutagenic potential of hydroxychloroquine was not evaluated. However, chloroquine has been shown to be a catalytic inhibitor of DNA repair enzymes (topoisomerase II) and to produce weak genotoxic effects through this mode of action.

USE IN SPECIFIC POPULATIONS

Pregnancy

Teratogenic Effects: Human pregnancies resulting in live births have been reported in the literature and no increase in the rate of birth defects has been demonstrated. Embryonic deaths and malformations of anophthalmia and microphthalmia in the offspring have been reported when pregnant rats received large doses of chloroquine.

NURSING MOTHERS

Nursing Mothers: Caution should be exercised when administering PLAQUENIL to nursing women. It has been demonstrated that hydroxychloroquine administered to nursing women is excreted in human milk and it is known that infants are extremely sensitive to the toxic effects of 4-aminoquinolines.

PEDIATRIC USE

Pediatric Use: Safety and efficacy have not been established in the chronic use of PLAQUENIL for systemic lupus erythematosus and juvenile idiopathic arthritis in children. Children are especially sensitive to the 4-aminoquinoline compounds. Most reported fatalities followed the accidental ingestion of chloroquine, sometimes in small doses (0.75 g or 1 g in one 3-year-old child). Patients should be strongly warned to keep these drugs out of the reach of children (see OVERDOSAGE).

GERIATRIC USE

Geriatric Use: Clinical studies of PLAQUENIL did not include sufficient numbers of subjects aged 65 and over to determine whether they respond differently from younger subjects. However, this drug is known to be substantially excreted by the kidney, and the risk of toxic reactions to this drug may be greater in patients with impaired renal function. Because elderly patients are more likely to have decreased renal function, care should be taken in dose selection and it may be useful to monitor renal function.

ADVERSE REACTIONS

The following adverse reactions have been identified during post-approval use of PLAQUENIL or other 4-aminoqunoline compounds. Because these reactions are reported voluntarily from a population of uncertain size, it is not always possible to reliably estimate their frequency or establish a causal relationship to drug exposure.

Blood and lymphatic system disorders: Bone marrow failure, anemia, aplastic anemia, agranulocytosis, leukopenia, and thrombocytopenia. Hemolysis reported in individuals with glucose-6-phosphate dehydrogenase (G-6-PD) deficiency.

Cardiac disorders: Cardiomyopathy which may result in cardiac failure and in some cases a fatal outcome (see WARNINGS and OVERDOSAGE). PLAQUENIL prolongs the QT interval. Ventricular arrhythmias and torsade de pointes have been reported in patients taking PLAQUENIL (see OVERDOSAGE and DRUG INTERACTIONS).

Ear and labyrinth disorders: Vertigo, tinnitus, nystagmus, nerve deafness, deafness.

Eye disorders: Irreversible retinopathy with retinal pigmentation changes (bull’s eye appearance), visual field defects (paracentral scotomas) and visual disturbances (visual acuity), maculopathies (macular degeneration), decreased dark adaptation, color vision abnormalities, corneal changes (edema and opacities) including corneal deposition of drug with or without accompanying symptoms (halo around lights, photophobia, blurred vision).

Gastrointestinal disorders: Nausea, vomiting, diarrhea, and abdominal pain.

General disorders and administration site conditions: Fatigue.

Hepatobiliary disorders: Liver function tests abnormal, hepatic failure acute.

Immune system disorders: Urticaria, angioedema, bronchospasm

Metabolism and nutrition disorders: Decreased appetite, hypoglycemia, porphyria, weight decreased.

Musculoskeletal and connective tissue disorders: Sensorimotor disorder, skeletal muscle myopathy or neuromyopathy leading to progressive weakness and atrophy of proximal muscle groups, depression of tendon reflexes and abnormal nerve conduction.

Nervous system disorders: Headache, dizziness, seizure, ataxia and extrapyramidal disorders such as dystonia, dyskinesia, and tremor have been reported with this class of drugs.

Psychiatric disorders: Affect/emotional lability, nervousness, irritability, nightmares, psychosis, suicidal behavior.

Skin and subcutaneous tissue disorders: Rash, pruritus, pigmentation disorders in skin and mucous membranes, hair color changes, alopecia. Dermatitis bullous eruptions including erythema multiforme, Stevens-Johnson syndrome, and toxic epidermal necrolysis, drug reaction with eosinophilia and systemic symptoms (DRESS syndrome), photosensitivity, dermatitis exfoliative, acute generalized exanthematous pustulosis (AGEP). AGEP has to be distinguished from psoriasis, although PLAQUENIL may precipitate attacks of psoriasis. It may be associated with pyrexia and hyperleukocytosis.

To report SUSPECTED ADVERSE REACTIONS, contact Concordia Pharmaceuticals at 1-877-370-1142 or FDA at 1-800-FDA-1088 or www.fda.gov/medwatch.

OVERDOSAGE

The 4-aminoquinoline compounds are very rapidly and completely absorbed after ingestion, and in accidental overdosage, or rarely with lower doses in hypersensitive patients, toxic symptoms may occur within 30 minutes. The symptoms of overdosage may include headache, drowsiness, visual disturbances, cardiovascular collapse, convulsions, hypokalemia, rhythm and conduction disorders including QT prolongation, torsades de pointes, ventricular tachycardia and ventricular fibrillation, followed by sudden potentially fatal respiratory and cardiac arrest. Treatment is symptomatic and must be prompt. Immediate gastric lavage until the stomach is completely emptied is indicated. After lavage, activated charcoal is introduced by the stomach tube within 30 minutes of ingestion of the drug may inhibit further intestinal absorption. To be effective, the dose of activated charcoal should be at least five times the estimated dose of hydroxychloroquine ingested.

Consideration should be given to administering diazepam parenterally since studies suggest that it may be beneficial in reversing chloroquine and hydroxychloroquine cardiotoxicity.

Respiratory support and shock management should be instituted as necessary.

Exchange transfusions are used to reduce the level of 4-aminoquinoline drug in the blood.

A patient who survives the acute phase and is asymptomatic should be closely observed for at least six hours. Fluids may be forced and sufficient ammonium chloride (8 g daily in divided doses for adults) may be administered for a few days to acidify the urine. This will promote urinary excretion in cases of both overdosage and sensitivity. However, caution must be exercised in patients with impaired renal function and/or metabolic acidosis.

DOSAGE AND ADMINISTRATION

One PLAQUENIL tablet contains 200 mg of hydroxychloroquine sulfate, which is equivalent to 155 mg base.

Take PLAQUENIL with a meal or a glass of milk.

Malaria

Prophylaxis
Adults: 400 mg (310 mg base) once weekly on the same day of each week starting 2 weeks prior to exposure, and continued for 4 weeks after leaving the endemic area.

Weight-based dosing in adults and pediatric patients: 6.5 mg/kg (5 mg/kg base), not to exceed 400 mg (310 mg base), once weekly on the same day of the week starting 2 weeks prior to exposure, and continued for 4 weeks after leaving the endemic area.

Treatment of Uncomplicated Malaria
Adults: 800 mg (620 mg base) followed by 400 mg (310 mg base) at 6 hours, 24 hours and 48 hours after the initial dose (total 2000 mg hydroxychloroquine sulfate or 1550 mg base).

Weight based dosage in adults and pediatric patients: 13 mg/kg (10 mg/kg base), not to exceed 800 mg (620 mg base) followed by 6.5 mg/kg (5 mg/kg base), not to exceed 400 mg (310 mg base), at 6 hours, 24 hours and 48 hours after the initial dose. PLAQUENIL film-coated tablets cannot be divided, therefore they should not be used to treat patients who weigh less than 31 kg.

For radical cure of P. vivax and P. malariae infections, concomitant therapy with an 8-aminoquinoline compound is necessary.

Lupus Erythematosus

The recommended adult dosage is 200 to 400 mg (155 to 310 mg base) daily, administered as a single daily dose or in two divided doses. Doses above 400 mg a day are not recommended.

The incidence of retinopathy has been reported to be higher when this maintenance dose is exceeded.

Rheumatoid Arthritis

The action of hydroxychloroquine is cumulative and may require weeks to months to achieve the maximum therapeutic effect (see CLINICAL PHARMACOLOGY).

Initial adult dosage: 400 mg to 600 mg (310 to 465 mg base) daily, administered as a single daily dose or in two divided doses. In a small percentage of patients, side effects may require temporary reduction of the initial dosage.

Maintenance adult dosage: When a good response is obtained, the dosage may be reduced by 50 percent and continued at a maintenance level of 200 mg to 400 mg (155 to 310 mg base) daily, administered as a single daily dose or in two divided doses.

Do not exceed 600 mg or 6.5 mg/kg (5 mg/kg base) per day, whichever is lower, as the incidence of retinopathy has been reported to be higher when this maintenance dose is exceeded.

Corticosteroids and salicylates may be used in conjunction with PLAQUENIL, and they can generally be decreased gradually in dosage or eliminated after a maintenance dose of PLAQUENIL has been achieved.

HOW SUPPLIED

PLAQUENIL tablets are white, to off-white, film coated tablets imprinted “PLAQUENIL” on one face in black ink. Each tablet contains 200 mg hydroxychloroquine sulfate (equivalent to 155 mg base).
Bottles of 60 tablets with child resistant closure (NDC 59212-562-60).
Bottles of 100 tablets with child resistant closure (NDC 59212-562-10).
Do not crush or divide PLAQUENIL film-coated tablets (see DOSAGE AND ADMINISTRATION).

Dispense in a tight, light-resistant container as defined in the USP/NF. Keep out of the reach of children.

Store at room temperature [20° to 25°C (68° to 77°F), allows excursions between 15° and 30°C (59° and 86°F)].

Mfd. for:
Concordia Pharmaceuticals
Distributed by:
Amdipharm Limited
17 Northwood House
Dublin 9, Ireland
Rev. 09/19
©2015 All rights reserved.

PRINCIPAL DISPLAY PANEL - 100 Tablet Bottle

NDC 59212-562-10
Rx only

Plaquenil®
hydroxychloroquine sulfate tablets, USP
200 mg

100 tablets

KEEP OUT OF THE REACH OF CHILDREN
Dispense in a tight, light-resistant container as defined in the USP/NF.

Concordia Pharmaceuticals

PRINCIPAL DISPLAY PANEL - 60 Tablet Bottle

NDC 59212-562-60
Rx only

Plaquenil®
hydroxychloroquine sulfate tablets, USP
200 mg

60 tablets

KEEP OUT OF THE REACH OF CHILDREN
Dispense in a tight, light-resistant container as defined in the USP/NF.

Concordia Pharmaceuticals